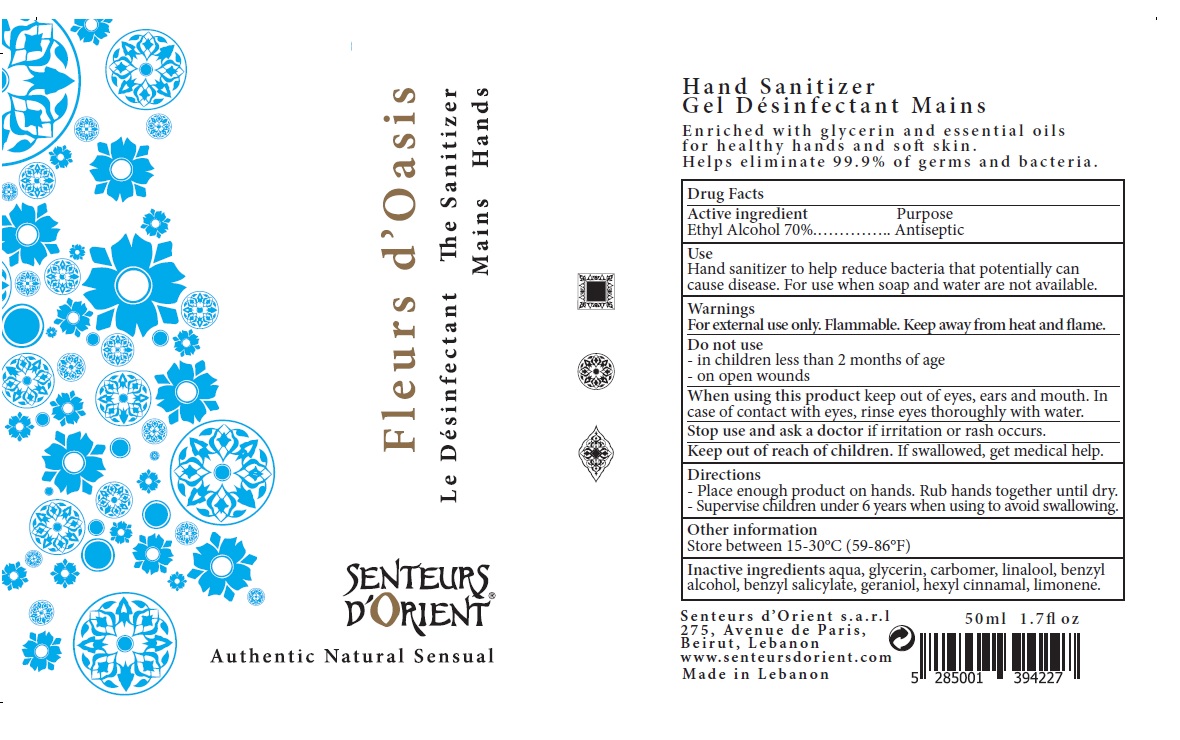 DRUG LABEL: SENTEURS DORIENT Hand Sanitizer
NDC: 79958-452 | Form: GEL
Manufacturer: SENTEURS D'ORIENT SARL
Category: otc | Type: HUMAN OTC DRUG LABEL
Date: 20201223

ACTIVE INGREDIENTS: ALCOHOL 70 mL/100 mL
INACTIVE INGREDIENTS: WATER; GLYCERIN; CARBOMER HOMOPOLYMER, UNSPECIFIED TYPE; LINALOOL, (+/-)-; BENZYL ALCOHOL; BENZYL SALICYLATE; GERANIOL; .ALPHA.-HEXYLCINNAMALDEHYDE; LIMONENE, (+)-

SENTEURS D'ORIENT® The Sanitizer Hands

Active ingredient

Ethyl Alcohol 70%

Purpose

Antiseptic

Use

Hand sanitizer to help reduce bacteria that potentially can cause disease. For use when soap and water are not available.

Warnings

For external use only. Flammable. Keep away from heat and flame.

Do not use

- in children less than 2 months of age
- on open wounds

When using this product keep out of eyes, ears and mouth. In case of contact with eyes, rinse eyes thoroughly with water.

Stop use and ask a doctor if irritation or rash occurs.

Keep out of reach of children. If swallowed, get medical help.

Directions

- Place enough product on hands. Rub hands together until dry.
- Supervise children under 6 years when using to avoid swallowing.

Other information

Store between 15-30°C (59-86°F)

Inactive ingredients

aqua, glycerin, carbomer, linalool, benzyl alcohol, benzyl salicylate, geraniol, hexyl cinnamal, limonene.

Authentic Natural Sensual

Enriched with glycerin and essential oils for healthy hands and soft skin.

Helps eliminate 99.9% of germs and bacteria.

Senteurs d'Orient s.a.r.l

275, Avenue de Paris,

Beirut, Lebanon

www.senteursdorient.com

Made in Lebanon